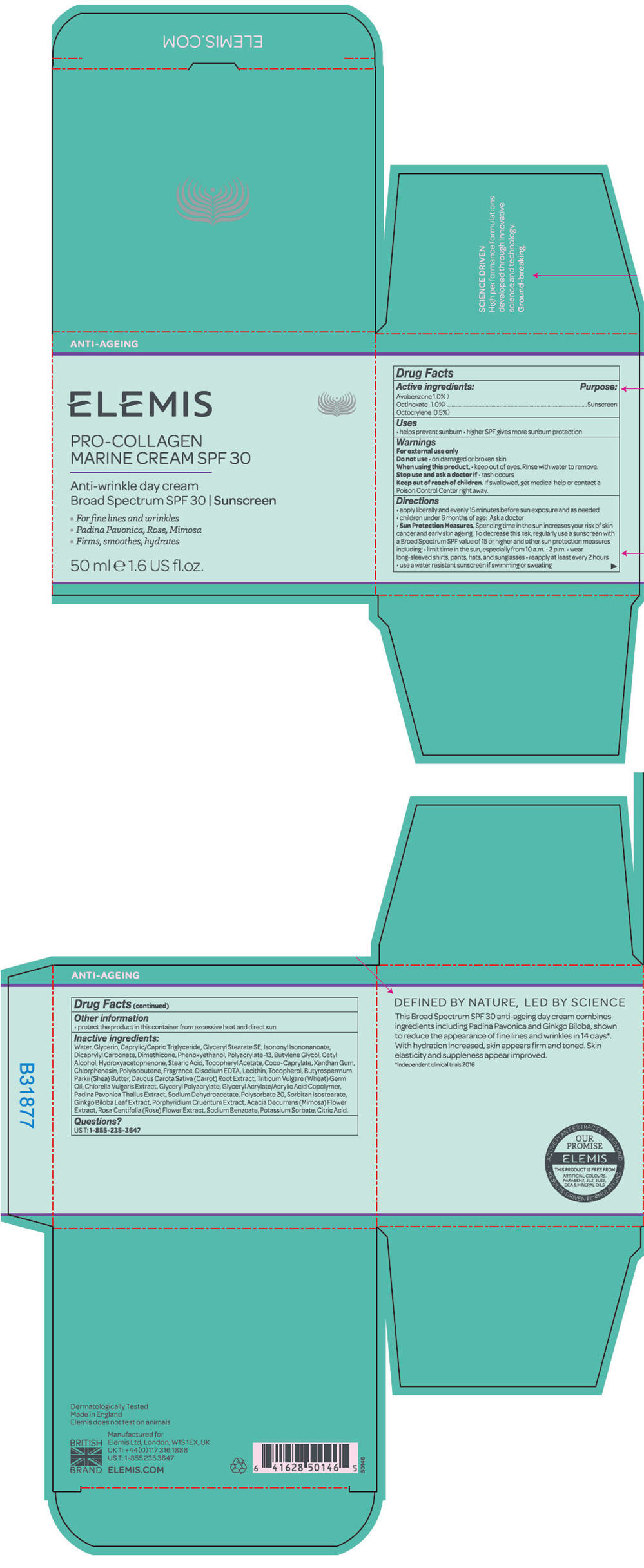 DRUG LABEL: Pro-Collagen Marine
NDC: 65912-001 | Form: CREAM
Manufacturer: ELEMIS Limited
Category: otc | Type: HUMAN OTC DRUG LABEL
Date: 20251119

ACTIVE INGREDIENTS: AVOBENZONE 10 mg/1 g; OCTINOXATE 10 mg/1 g; OCTOCRYLENE 5 mg/1 g
INACTIVE INGREDIENTS: LEUCONOSTOC/RADISH ROOT FERMENT FILTRATE; WHEY PROTEIN HYDROLYSATE; WATER; GLYCERIN; MEDIUM-CHAIN TRIGLYCERIDES; GLYCERYL STEARATE SE; ISONONYL ISONONANOATE; DICAPRYLYL CARBONATE; DIMETHICONE; PHENOXYETHANOL; BUTYLENE GLYCOL; CETYL ALCOHOL; HYDROXYACETOPHENONE; STEARIC ACID; .ALPHA.-TOCOPHEROL ACETATE; COCO-CAPRYLATE; XANTHAN GUM; CHLORPHENESIN; POLYISOBUTYLENE (1000 MW); EDETATE DISODIUM ANHYDROUS; LECITHIN, SOYBEAN; TOCOPHEROL; SHEA BUTTER; CARROT; WHEAT GERM OIL; CHLORELLA VULGARIS; PADINA PAVONICA; SODIUM DEHYDROACETATE; POLYSORBATE 20; SORBITAN ISOSTEARATE; GINKGO; PORPHYRIDIUM PURPUREUM; ACACIA DECURRENS FLOWER; ROSA CENTIFOLIA FLOWER; SODIUM BENZOATE; POTASSIUM SORBATE; CITRIC ACID MONOHYDRATE

Pro-Collagen Marine
Broad Spectrum SPF 30

Drug Facts

Active ingredients

Avobenzone 1.0% }
Octinoxate 1.0%}
Octocrylene 0.5%}

Purpose

Sunscreen

Uses

- helps prevent sunburn
- higher SPF gives more sunburn protection

Warnings

For external use only

Do not use

- on damaged or broken skin

When using this product,

- keep out of eyes. Rinse with water to remove.

Stop use and ask a doctor if

- rash occurs

Keep out of reach of children. If swallowed, get medical help or contact a Poison Control Center right away.

Directions

- apply liberally and evenly 15 minutes before sun exposure and as needed
- children under 6 months of age: Ask a doctor
- Sun Protection Measures. Spending time in the sun increases your risk of skin cancer and early skin ageing. To decrease this risk, regularly use a sunscreen with a Broad Spectrum SPF value of 15 or higher and other sun protection measures including:
  - limit time in the sun, especially from 10 a.m. - 2 p.m.
  - wear long-sleeved shirts, pants, hats, and sunglasses
  - reapply at least every 2 hours
  - use a water resistant sunscreen if swimming or sweating

Other information

- protect the product in this container from excessive heat and direct sun

Inactive ingredients

AQUA/WATER/EAU
GLYCERIN
CAPRYLIC/CAPRIC TRIGLYCERIDE
GLYCERYL STEARATE SE
ISONONYL ISONONANOATE
DICAPRYLYL CARBONATE
DIMETHICONE
BUTYL METHOXYDIBENZOYLMETHANE
ETHYLHEXYL METHOXYCINNAMATE
PHENOXYETHANOL
POLYACRYLATE-13
BUTYLENE GLYCOL
CETYL ALCOHOL
HYDROXYACETOPHENONE
STEARIC ACID
TOCOPHERYL ACETATE
COCO-CAPRYLATE
XANTHAN GUM
CHLORPHENESIN
POLYISOBUTENE
FRAGRANCE (PARFUM)
DISODIUM EDTA
TOCOPHEROL
BUTYROSPERMUM PARKII (SHEA)
BUTTER
TRITICUM VULGARE (WHEAT) GERM OIL
CHLORELLA VULGARIS EXTRACT
GLYCERYL POLYACRYLATE
DAUCUS CAROTA SATIVA (CARROT) ROOT EXTRACT
GLYCERYL ACRYLATE/ACRYLIC ACID COPOLYMER
LECITHIN
PADINA PAVONICA THALLUS EXTRACT
SODIUM DEHYDROACETATE
POLYSORBATE 20
SORBITAN ISOSTEARATE
GINKGO BILOBA LEAF EXTRACT
INGREDIENT NAME
PORPHYRIDIUM CRUENTUM EXTRACT
MIMOSA TENUIFLORA BARK EXTRACT
ROSA DAMASCENA FLOWER
EXTRACT
COLLAGEN AMINO ACIDS
LEUCONOSTOC/RADISH ROOT FERMENT FILTRATE
POTASSIUM SORBATE
SODIUM BENZOATE
CITRIC ACID

Questions?

US T: 1-855-235-3647